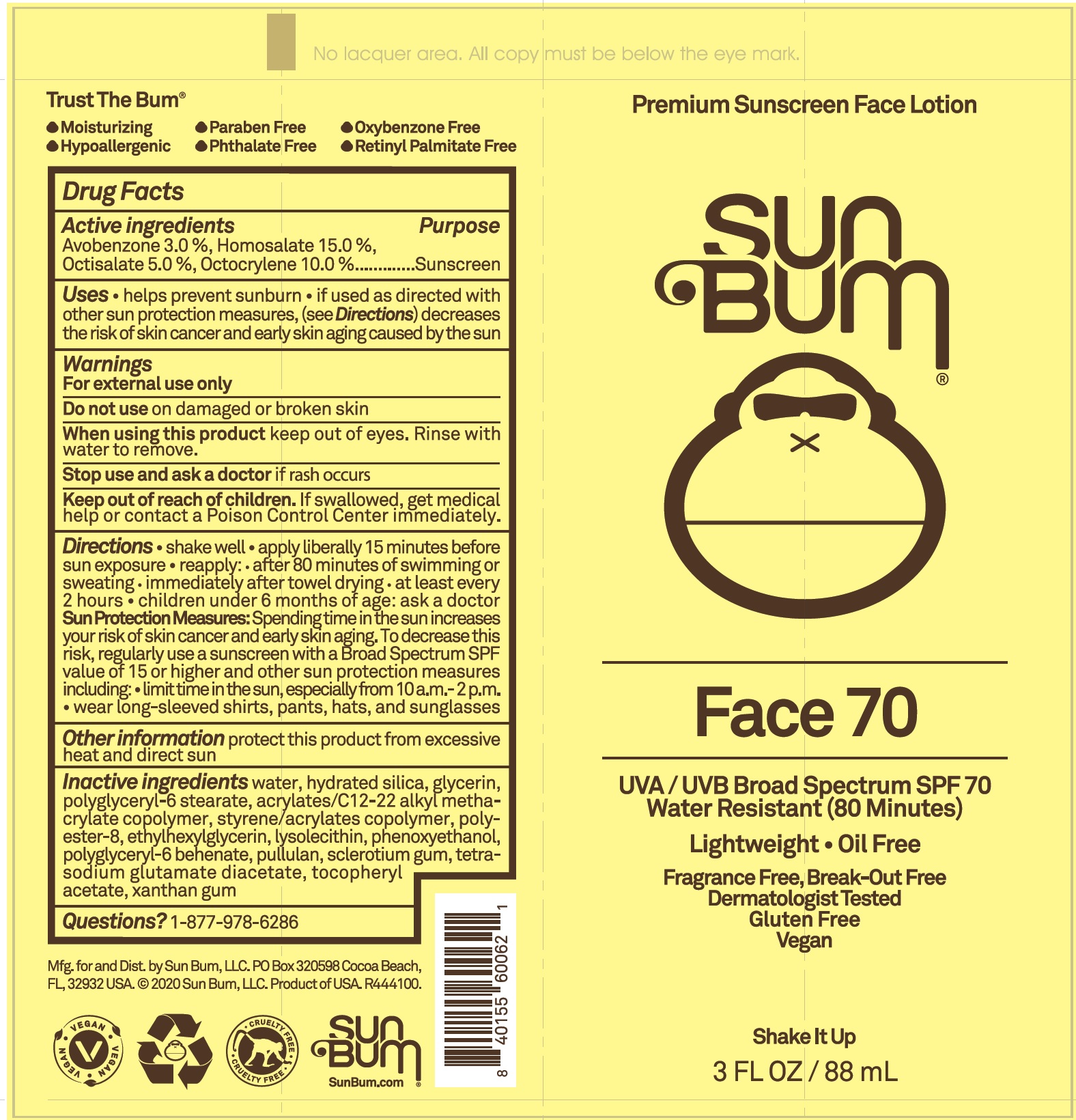 DRUG LABEL: Sun Bum Face SPF 70
NDC: 69039-618 | Form: LOTION
Manufacturer: Sun Bum LLC
Category: otc | Type: HUMAN OTC DRUG LABEL
Date: 20220204

ACTIVE INGREDIENTS: AVOBENZONE 30 mg/1 mL; HOMOSALATE 150 mg/1 mL; OCTISALATE 50 mg/1 mL; OCTOCRYLENE 100 mg/1 mL
INACTIVE INGREDIENTS: WATER; HYDRATED SILICA; GLYCERIN; POLYGLYCERYL-6 STEARATE; ETHYLHEXYLGLYCERIN; PHENOXYETHANOL; POLYGLYCERYL-6 BEHENATE; PULLULAN; BETASIZOFIRAN; TETRASODIUM GLUTAMATE DIACETATE; .ALPHA.-TOCOPHEROL ACETATE; XANTHAN GUM

Sun Bum Face SPF 70

Active ingredients

Avobenzone 3.0%, Homosalate 15.0%, Octisalate 5.0%, Octocrylene 10.0%.

Purpose

Sunscreen

Uses

- helps prevent sunburn
- if used as directed with other sun protection measures (see Directions), decreases the risk of skin cancer and early skin aging caused by the sun

Warnings

For externel use only

Do not use

on damaged or broken skin

When using this product

keep out of eyes. Rinse with water to remove.

Stop use and ask a doctor

if rash occurs

Keep out of reach of children.

If swallowed, get medical help or contact a Poison Control Center right away.

Directions

- shake well
- apply liberally 15 minutes before sun exposure
- reapply:
- after 80 minutes of swimming or sweating
- immediately after towel drying
- at least every 2 hours
- children under 6 months of age:ask a doctor
- Sun Protection Measures. Spending time in the sun increases your risk of skin cancer and early skin aging. To decrease this risk, regularly use a sunscreen with a Broad Spectrum SPF value of 15 or higher and other sun protection measures including:
- limit time in the sun, especially from 10a.m. - 2.p.m.
- wear long-sleeve shirts, pants, hats, and sunglasses.

Other information

- protect this product from excessive heat and direct sun

Inactive ingredients

water, hydrated silica, glycerin, polyglyceryl-6 stearate, acrylates/C12-22 alkyl methacrylate copolymer, styrene/acrylates copolymer, polyester-8, ethylhexylglycerin, lysolecithin, phenoxyethanol, polyglyceryl-6 behenate, pullulan, sclerotium gum, tetra sodium glutamate diacetate, tocopheryl acetate, xanthan gum

Questions?

1-877-978-6286